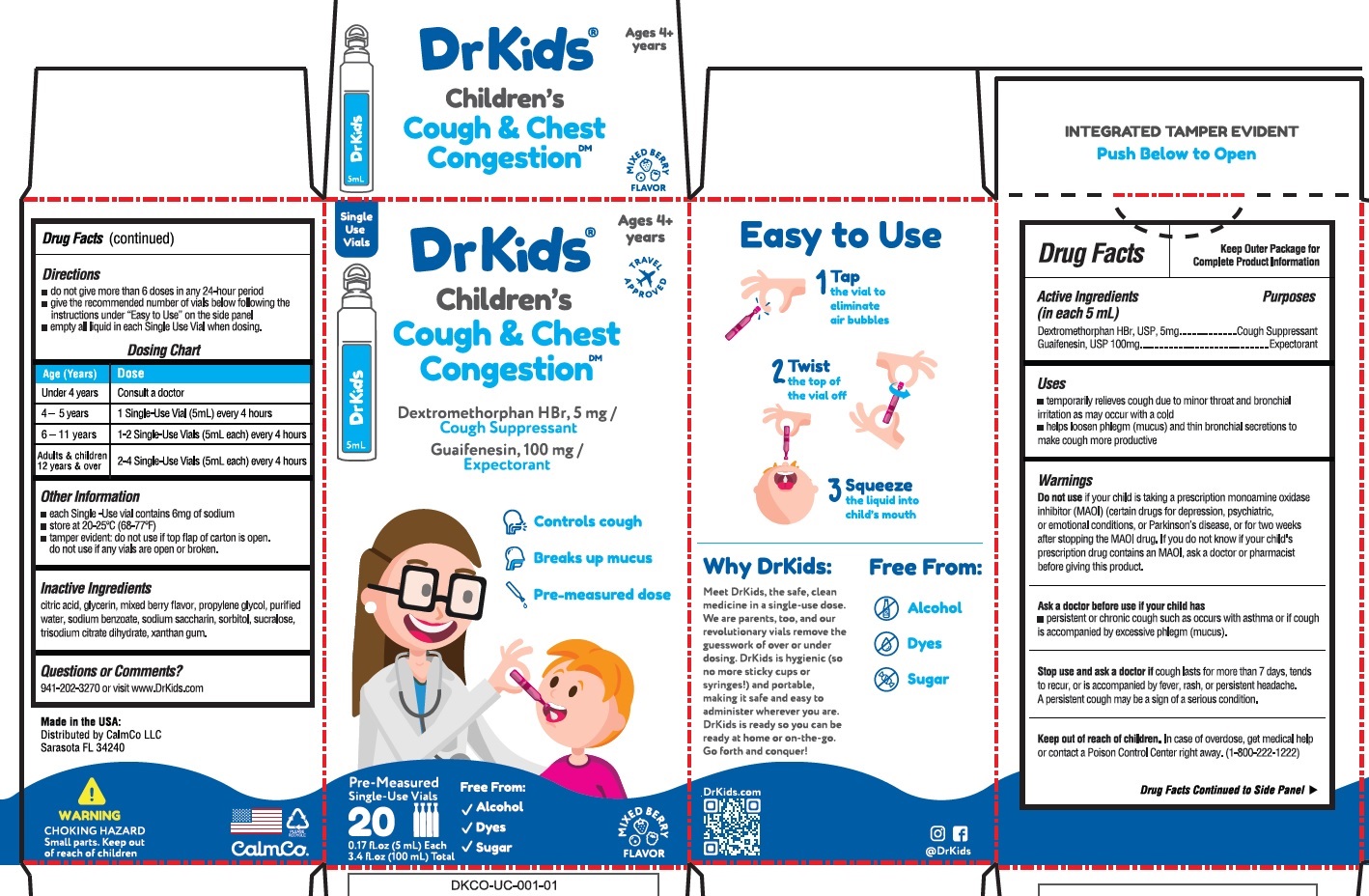 DRUG LABEL: DrKids Childrens Cough and Chest Congestion DM
NDC: 73282-0013 | Form: SOLUTION
Manufacturer: CalmCo LLC
Category: otc | Type: HUMAN OTC DRUG LABEL
Date: 20240524

ACTIVE INGREDIENTS: DEXTROMETHORPHAN HYDROBROMIDE 5 mg/5 mL; GUAIFENESIN 100 mg/5 mL
INACTIVE INGREDIENTS: WATER; TRISODIUM CITRATE DIHYDRATE; SORBITOL; CITRIC ACID MONOHYDRATE; SACCHARIN SODIUM; SUCRALOSE; XANTHAN GUM; SODIUM BENZOATE; GLYCERIN; PROPYLENE GLYCOL

DrKids Children’s Cough & Chest Congestion DM

Active Ingredient (in each 5mL)

Dextromethorphan HBr, USP, 5mg

Guaifenesin, USP, 100mg

Purpose

Cough suppressant

Expectorant

Uses

- temporarily relieves cough due to minor throat and bronchial irritation as may occur with a cold
- helps loosen phlegm (mucus) and thin bronchial secretions to make cough more productive

Warnings

Do not use

if your child is taking a prescription monoamine oxidase inhibitor (MAOI) (certain drugs for depression, psychiatric, or emotional conditions, or Parkinson’s disease), or for two weeks after stopping the MAOI drug. If you do not know if your child’s prescription drug contains an MAOI, ask a doctor or pharmacist before giving this product.

Ask a doctor before use if your child has

persistent or chronic cough such as occurs with asthma or if cough is accompanied by excessive phlegm (mucus).

Stop use and ask a doctor if

cough lasts for more than 7 days, tends to recur, or is accompanied by fever, rash, or persistent headache. A persistent cough may be a sign of a serious condition.

OVERDOSAGE

In case of overdose, get medical help or contact a Poison Control Center right away. (1-800-222-1222)

Directions

do not give more than 6 doses in any 24 hour period
give the recommended number of vials below, following the instructions under How to Open and Use on the side panel
empty all liquid in each Single-Use Vial when dosing

Dosing Chart

Age (Years) | Dose
under 4 years | Consult a doctor
4 – 5 years | 1 Single-Use Vial (5 mL) every 4 hours
6 – 11 years | 1 – 2 Single-Use Vials (5 mL each) every 4 hours
Adults and children 12 years and over | 2 – 4 Single-Use Vials (5 mL each) every 4 hours

Inactive Ingredients

citric acid, glycerin, mixed berry flavor, propylene glycol, purified water, sodium benzoate, sodium saccharin, sorbitol, sucralose, trisodium citrate dihydrate, xanthan gum

Other information

- each Single-Use vial contains 6mg of sodium
- store at 20-25ºC (68-77ºF)
- tamper evident: do not use if top flap of carton is open. Do not use if any vials are open or broken

Questions or comments?

941-202-3270 or visit www.DrKids.com